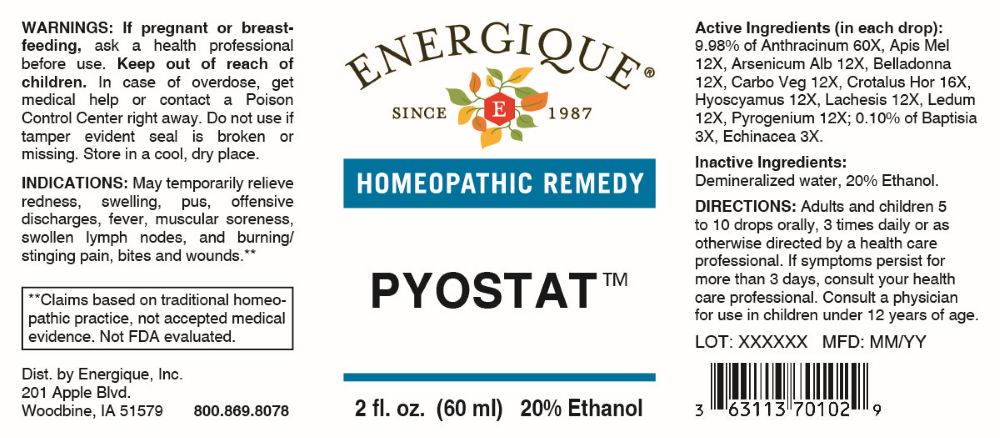 DRUG LABEL: Pyostat
NDC: 44911-0900 | Form: LIQUID
Manufacturer: Energique, Inc.
Category: homeopathic | Type: HUMAN OTC DRUG LABEL
Date: 20260106

ACTIVE INGREDIENTS: BAPTISIA TINCTORIA ROOT 3 [hp_X]/1 mL; ECHINACEA ANGUSTIFOLIA WHOLE 3 [hp_X]/1 mL; BACILLUS ANTHRACIS IMMUNOSERUM RABBIT 60 [hp_X]/1 mL; ARSENIC TRIOXIDE 12 [hp_X]/1 mL; ATROPA BELLADONNA 12 [hp_X]/1 mL; CROTALUS HORRIDUS HORRIDUS VENOM 16 [hp_X]/1 mL; HYOSCYAMUS NIGER 12 [hp_X]/1 mL; LACHESIS MUTA VENOM 12 [hp_X]/1 mL; RANCID BEEF 12 [hp_X]/1 mL; APIS MELLIFERA 12 [hp_X]/1 mL; ACTIVATED CHARCOAL 12 [hp_X]/1 mL; RHODODENDRON TOMENTOSUM LEAFY TWIG 12 [hp_X]/1 mL
INACTIVE INGREDIENTS: WATER; ALCOHOL

DRUG FACTS:

ACTIVE INGREDIENTS:

(in each drop): 9.98% of Anthracinum 60X, Apis Mellifica 12X, Arsenicum Album 12X, Belladonna 12X, Carbo Vegetabilis 12X, Crotalus Horridus 16X, Hyoscyamus Niger 12X, Lachesis Mutus 12X, Ledum Palustre 12X, Pyrogenium 12X; 0.10% of Baptisia Tinctoria 3X, Echinacea 3X.

PURPOSE:

May temporarily relieve redness, swelling, pus, offensive discharges, fever, muscular soreness, swollen lymph nodes, and burning/stinging pain, bites, and wounds.**

**Claims based on traditional homeopathic practice, not accepted medical evidence. Not FDA evaluated.

WARNINGS:

If pregnant or breast-feeding, ask a health professional before use.

Keep out of reach of children. In case of overdose, get medical help or contact a Poison Control Center right away.

Do not use if tamper evident seal is broken or missing.

Store in a cool, dry place.

KEEP OUT OF REACH OF CHILDREN:

In case of overdose, get medical help or contact a Poison Control Center right away.

DIRECTIONS:

Adults and children 5 to 10 drops orally, 3 times daily or as otherwise directed by a health care professional. If symptoms persist for more than 3 days, consult your health care professional. Consult a physician for use in children under 12 years of age.

INDICATIONS:

May temporarily relieve redness, swelling, pus, offensive discharges, fever, muscular soreness, swollen lymph nodes, and burning/stinging pain, bites, and wounds.**

**Claims based on traditional homeopathic practice, not accepted medical evidence. Not FDA evaluated.

INACTIVE INGREDIENTS:

Demineralized water, 20% Ethanol.

QUESTIONS:

Dist. by Energique, Inc.

201 Apple Blvd.
Woodbine, IA 51579

800.869.8078

PACKAGE LABEL DISPLAY:

ENERGIQUE
SINCE 1987
HOMEOPATHIC REMEDY
PYOSTAT
2 fl. oz. (60 ml)